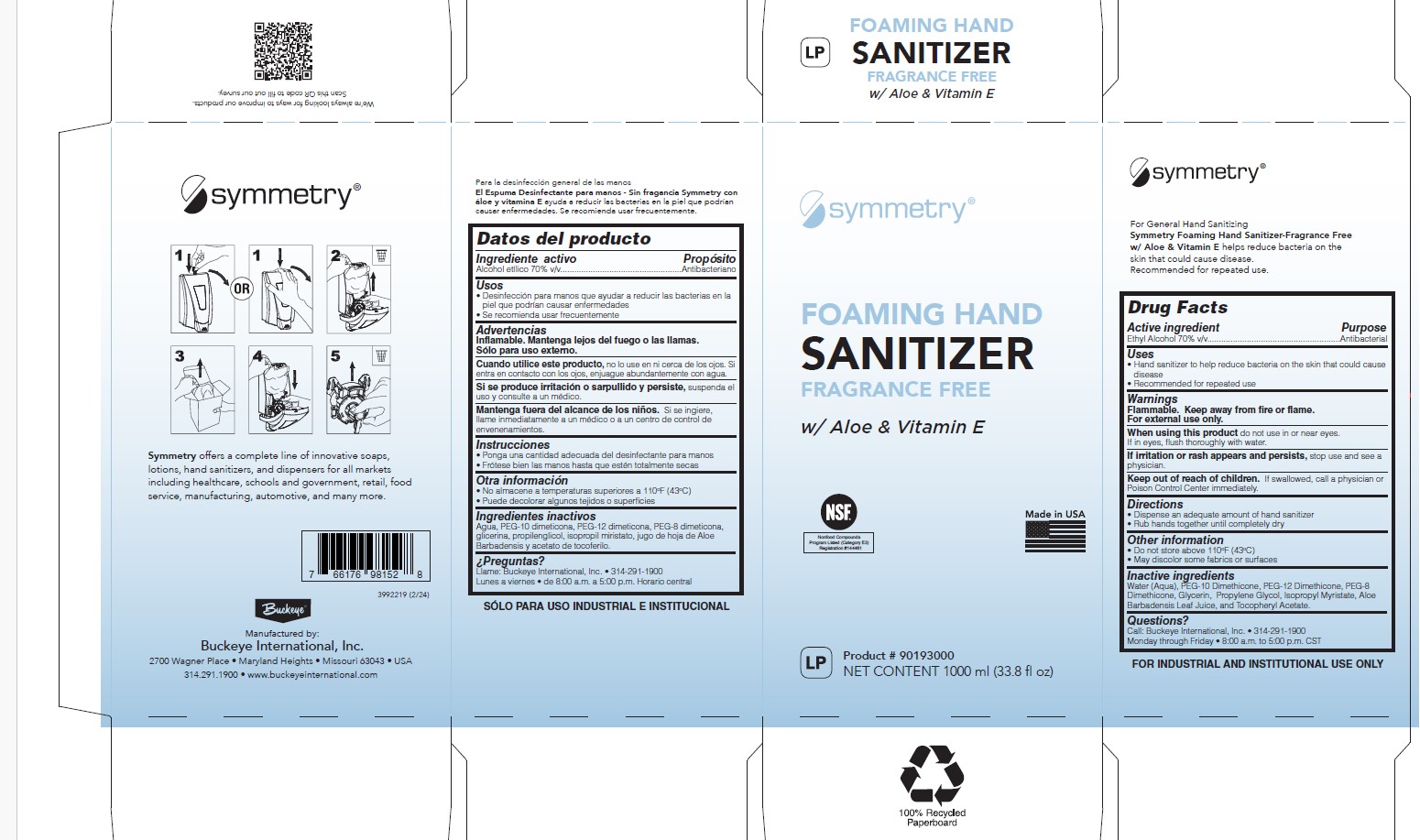 DRUG LABEL: Symmetry Foaming Hand Sanitizer Fragrance Free
NDC: 30805-020 | Form: LIQUID
Manufacturer: Buckeye International, Inc.
Category: otc | Type: HUMAN OTC DRUG LABEL
Date: 20250327

ACTIVE INGREDIENTS: ALCOHOL 70 mL/100 mL
INACTIVE INGREDIENTS: WATER; GLYCERIN; PEG-8 DIMETHICONE; ALOE VERA LEAF; PEG-12 DIMETHICONE (300 CST); PROPYLENE GLYCOL; .ALPHA.-TOCOPHEROL ACETATE; PEG-10 DIMETHICONE (600 CST); ISOPROPYL MYRISTATE

30805-20

Active ingredient

Ethyl Alcohol 70% v/v

Purpose

Antibacterial

Uses

- Hand sanitizer to help reduce bacteria on the skin that could cause disease
- Recommendend for repeated use

Warnings

Flammable. Keep away from fire or flame.

For external use only.

WHEN USING

When using this productdo not use in or near eyes.

If in eyes, flush thoroughly with water.

STOP USE

If irritation or rash appears and persists,stop use and see a physician.

KEEP OUT OF REACH OF CHILDREN

Keep out of reach of chidren.If swallowed, call a physician or Poison Control Center Immediately.

Directions

- Dispense an adequate amount of hand sanitizer
- Rub hands together until completely dry

Other information

- Do not store above 110°F (43°C)
- May discolor some fabrics or surfaces

Inactive ingredients

Water (Aqua), PEG-10 Dimethicone, PEG-12 Dimethicone, PEG-8 Dimethicone, Glycerin, Propylene Glycol, Isopropyl Myristate, Aloe Barbadensis Leaf Juice, and Tocopheryl Acetate.

Questions?

Call: Buckeye International, Inc. • 314-291-1900

Monday through Friday • 8:00 a.m. to 5:00 p.m. CST

PACKAGE LABEL

symmetry

FOAMING HAND

SANITIZER

FRAGRANCE FREE

w/Aloe & Vitamin E

NSF

Nonfood Compounds

Program Listed (Category E3)

Registration #144461

Made in USA

lP Product #90193000

NET CONTENTS 1000 ml (33.8 fl oz)